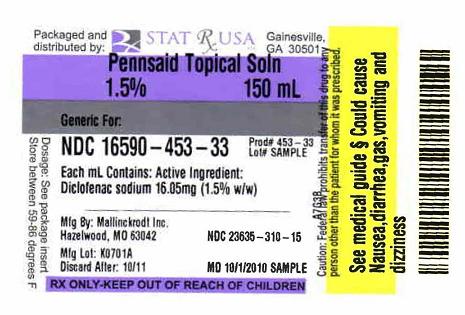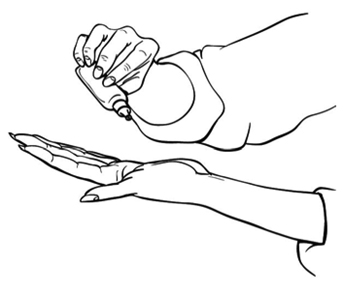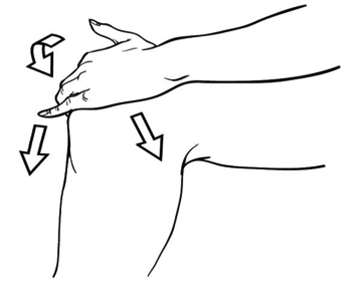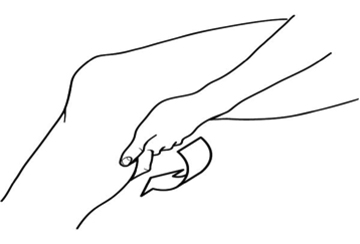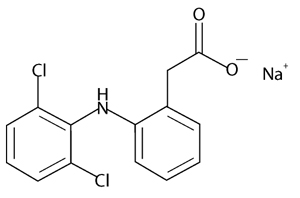 DRUG LABEL: PENNSAID
NDC: 16590-453 | Form: LIQUID
Manufacturer: STAT RX USA LLC
Category: prescription | Type: HUMAN PRESCRIPTION DRUG LABEL
Date: 20101001

ACTIVE INGREDIENTS: DICLOFENAC SODIUM 16.05 mg/1 mL
INACTIVE INGREDIENTS: DIMETHYL SULFOXIDE; PROPYLENE GLYCOL; ALCOHOL; GLYCERIN; WATER

HIGHLIGHTS OF PRESCRIBING INFORMATION

These highlights do not include all the information needed to use PENNSAID® safely and effectively. See full prescribing information for PENNSAID.
PENNSAID (diclofenac sodium topical solution) 1.5% w/w is for topical use only.
Initial U.S. Approval: 1988

WARNING: CARDIOVASCULAR AND GASTROINTESTINAL RISK

See full prescribing information for complete boxed warning.

Cardiovascular Risk

- Nonsteroidal anti-inflammatory drugs (NSAIDs) may cause an increased risk of serious cardiovascular thrombotic events, myocardial infarction, and stroke, which can be fatal. Patients with cardiovascular disease or risk factors for cardiovascular disease may be at greater risk. (5.1)
- PENNSAID is contraindicated for the treatment of perioperative pain in the setting of coronary artery bypass graft (CABG) surgery. (4)

Gastrointestinal Risk

- NSAIDs, including PENNSAID, cause an increased risk of serious gastrointestinal adverse events including bleeding, ulceration, and perforation of the stomach or intestines, which can be fatal. These events can occur at any time during use and without warning symptoms. Elderly patients are at greater risk for serious gastrointestinal events. (5.2)

1. INDICATIONS AND USAGE

PENNSAID is a nonsteroidal anti-inflammatory drug (NSAID) indicated for the treatment of signs and symptoms of osteoarthritis of the knee(s). (1)

2. DOSAGE AND ADMINISTRATION

For the relief of the signs and symptoms of osteoarthritis of the knee(s), the recommended dose is 40 drops on each painful knee, 4 times a day. (2)

- Apply PENNSAID to clean, dry skin. (2.1)
- Dispense PENNSAID 10 drops at a time either directly onto the knee or first into the hand and then onto the knee. Spread PENNSAID evenly around front, back and sides of the knee. Repeat this procedure until 40 drops have been applied and the knee is completely covered with solution. (2.1)
- Wash hands completely after administering the product.
- Wait until the area is completely dry before covering with clothing or applying sunscreen, insect repellent, cosmetics, topical medications, or other substances.
- Do not get PENNSAID in your eyes, nose or mouth.

3. DOSAGE FORMS AND STRENGTHS

- 1.5% w/w topical solution (3)

4. CONTRAINDICATIONS

- Known hypersensitivity to diclofenac sodium. (4)
- History of asthma, urticaria, or allergic-type reactions after taking aspirin or other NSAIDs. (4)
- Use in the perioperative period of coronary artery bypass graft (CABG) surgery. (4)

5. WARNINGS AND PRECAUTIONS

- Serious and potentially fatal cardiovascular thrombotic events, myocardial infarction, and stroke can occur with NSAID treatment. Use the lowest effective dose of PENNSAID in patients with known CV disease or risk factors for CV disease. (5.1)
- NSAIDs can cause serious gastrointestinal (GI) adverse events including inflammation, bleeding, ulceration, and perforation. Prescribe PENNSAID with caution in those with a prior history of ulcer disease or gastrointestinal bleeding. (5.2)
- Elevation of one or more liver tests may occur during therapy with NSAIDs. Discontinue PENNSAID immediately if abnormal liver tests persist or worsen. (5.3)
- Hypertension can occur with NSAID treatment. Monitor blood pressure closely with PENNSAID treatment. (5.4)
- Use PENNSAID with caution in patients with fluid retention or heart failure. (5.5)
- Long-term administration of NSAIDs can result in renal papillary necrosis and other renal injury. Use PENNSAID with caution in patients at greatest risk of this reaction, including the elderly, those with impaired renal function, heart failure, liver dysfunction, and those taking diuretics and ACE-inhibitors. (5.6)
- Anaphylactoid reactions may occur in patients with the aspirin triad or in patients without prior exposure to PENNSAID. (5.7)
- NSAIDs can cause serious skin adverse events such as exfoliative dermatitis, Stevens-Johnson Syndrome (SJS), and toxic epidermal necrolysis (TEN), which can be fatal. (5.8)
- Not for use during pregnancy. (5.9)
- Do not administer to patients with aspirin sensitive asthma and use with caution in patients with preexisting asthma. (5.10)
- Avoid exposure of treated knee(s) to natural or artificial sunlight. (5.11)
- Avoid contact of PENNSAID with eyes and mucosa. (5.12)
- Avoid concurrent use with oral NSAIDs. (5.13)

6. ADVERSE REACTIONS

The most common adverse events with PENNSAID are application site reactions. (6.1)
To report SUSPECTED ADVERSE REACTIONS, contact Mallinckrodt Brand Pharmaceuticals, Inc. at 1-800-778-7898 or FDA at 1-800-FDA-1088 or www.fda.gov/medwatch.

7. DRUG INTERACTIONS

- Concomitant administration of diclofenac and aspirin is not generally recommended because of the potential of increased adverse effects including increased GI bleeding. (7.1)
- Concomitant use of anticoagulants and diclofenac have a risk of serious GI bleeding higher than users of either drug alone. (7.2)

8. USE IN SPECIFIC POPULATIONS

- Pregnancy: Not recommended for use during pregnancy. (8.1)
- Nursing Mothers: Use with caution, as it is not known if diclofenac is excreted in human milk. (8.3)

FULL PRESCRIBING INFORMATION

WARNING: CARDIOVASCULAR AND GASTROINTESTINAL RISK

Cardiovascular Risk

- Nonsteroidal anti-inflammatory drugs (NSAIDs) may cause an increased risk of serious cardiovascular thrombotic events, myocardial infarction, and stroke, which can be fatal. This risk may increase with duration of use. Patients with cardiovascular disease or risk factors for cardiovascular disease may be at greater risk [see Warnings and Precautions (5.1)].
- PENNSAID is contraindicated in the perioperative setting of coronary artery bypass graft (CABG) surgery [see Contraindications (4)].

Gastrointestinal Risk

- NSAIDs cause an increased risk of serious gastrointestinal adverse events including bleeding, ulceration, and perforation of the stomach or intestines, which can be fatal. These events can occur at any time during use and without warning symptoms. Elderly patients are at greater risk for serious gastrointestinal events [see Warnings and Precautions (5.2)].

1. INDICATIONS AND USAGE

PENNSAID is a nonsteroidal anti-inflammatory drug (NSAID) indicated for the treatment of signs and symptoms of osteoarthritis of the knee(s).

2. DOSAGE AND ADMINISTRATION

2.1 General Instructions

For the relief of the signs and symptoms of osteoarthritis of the knee(s), the recommended dose is 40 drops per knee, 4 times a day.

Apply PENNSAID to clean, dry skin.

To avoid spillage, dispense PENNSAID 10 drops at a time either directly onto the knee or first into the hand and then onto the knee. Spread PENNSAID evenly around front, back and sides of the knee. Repeat this procedure until 40 drops have been applied and the knee is completely covered with solution.

To treat the other knee, if symptomatic, repeat the procedure.

Application of PENNSAID in an amount exceeding or less than the recommended dose has not been studied and is therefore not recommended.

2.2 Special Precautions

- Avoid showering/bathing for at least 30 minutes after the application of PENNSAID to the treated knee.
- Wash and dry hands after use.
- Do not apply PENNSAID to open wounds.
- Avoid contact of PENNSAID with eyes and mucous membranes.
- Do not apply external heat and/or occlusive dressings to treated knees.
- Avoid wearing clothing over the PENNSAID-treated knee(s) until the treated knee is dry.
- Protect the treated knee(s) from sunlight.
- Wait until the treated area is dry before applying sunscreen, insect repellant, lotion, moisturizer, cosmetics, or other topical medication to the same knee you have just treated with PENNSAID.

3. DOSAGE FORMS AND STRENGTHS

1.5% w/w topical solution

4. CONTRAINDICATIONS

PENNSAID is contraindicated in patients with a known hypersensitivity to diclofenac sodium or any other component of PENNSAID.

PENNSAID is contraindicated in patients who have experienced asthma, urticaria, or allergic-type reactions after taking aspirin or other NSAIDs. Severe, rarely fatal, anaphylactic-like reactions to NSAIDs have been reported in such patients [see Warnings and Precautions (5.7, 5.10)].

PENNSAID is contraindicated in the setting of coronary artery bypass graft (CABG) surgery [see Warnings and Precautions (5.1)].

5. WARNINGS AND PRECAUTIONS

5.1 Cardiovascular Thrombotic Events

Clinical trials of several oral COX-2 selective and nonselective NSAIDs of up to three years duration have shown an increased risk of serious cardiovascular (CV) thrombotic events, myocardial infarction (MI), and stroke, which can be fatal. All NSAIDs, including PENNSAID and COX-2 selective and nonselective orally administered NSAIDs, may have a similar risk. Patients with known CV disease or risk factors for CV disease may be at greater risk. To minimize the potential risk for an adverse CV event in patients treated with an NSAID, use the lowest effective dose for the shortest duration possible. Physicians and patients should remain alert for the development of such events, even in the absence of previous CV symptoms. Inform patients about the signs and/or symptoms of serious CV events and the steps to take if they occur.

Two large, controlled, clinical trials of an orally administered COX-2 selective NSAID for the treatment of pain in the first 10 to 14 days following CABG surgery found an increased incidence of myocardial infarction and stroke [see Contraindications (4)].

There is no consistent evidence that concurrent use of aspirin mitigates the increased risk of serious CV thrombotic events associated with NSAID use.
The concurrent use of aspirin and NSAIDs, such as diclofenac, does increase the risk of serious GI events [see Warnings and Precautions (5.2)].

5.2 Gastrointestinal Effects – Risk of GI Ulceration, Bleeding, and Perforation

NSAIDs, including diclofenac, can cause serious gastrointestinal (GI) adverse events including bleeding, ulceration, and perforation of the stomach, small intestine, or large intestine, which can be fatal. These serious adverse events can occur at any time, with or without warning symptoms, in patients treated with NSAIDs. Only one in five patients who develop a serious upper GI adverse event on NSAID therapy is symptomatic. Upper GI ulcers, gross bleeding, or perforation caused by NSAIDs occur in approximately 1% of patients treated for 3 to 6 months, and in about 2 to 4% of patients treated for one year. These trends continue with longer duration of use, increasing the likelihood of developing a serious GI event at some time during the course of therapy. However, even short-term therapy is not without risk.

Prescribe NSAIDs, including PENNSAID, with extreme caution in those with a prior history of ulcer disease or gastrointestinal bleeding. Patients with a prior history of peptic ulcer disease and/or gastrointestinal bleeding who use NSAIDs have a greater than 10-fold increased risk for developing a GI bleed compared to patients with neither of these risk factors. Other factors that increase the risk of GI bleeding in patients treated with NSAIDs include concomitant use of oral corticosteroids or anticoagulants, longer duration of NSAID therapy, smoking, use of alcohol, older age, and poor general health status. Most spontaneous reports of fatal GI events are in elderly or debilitated patients and therefore, use special care when treating this population.

To minimize the potential risk for an adverse GI event, use the lowest effective dose for the shortest possible duration. Remain alert for signs and symptoms of GI ulceration and bleeding during diclofenac therapy and promptly initiate additional evaluation and treatment if a serious GI adverse event is suspected. For high-risk patients, consider alternate therapies that do not involve NSAIDs.

5.3 Hepatic Effects

Borderline elevations (less than 3 times the upper limit of the normal [ULN] range) or greater elevations of transaminases occurred in about 15% of oral diclofenac-treated patients in clinical trials of indications other than acute pain. Of the markers of hepatic function, ALT (SGPT) is recommended for the monitoring of liver injury.

In clinical trials of an oral diclofenac-misoprostol combination product, meaningful elevations (i.e., more than 3 times the ULN) of AST (SGOT) occurred in about 2% of approximately 5,700 patients at some time during diclofenac treatment (ALT was not measured in all studies).

In an open-label, controlled trial of 3,700 patients treated for 2 to 6 months, patients with oral diclofenac were monitored first at 8 weeks and 1,200 patients were monitored again at 24 weeks. Meaningful elevations of ALT and/or AST occurred in about 4% of the 3,700 patients and included marked elevations (>8 times the ULN) in about 1% of the 3,700 patients. In this open-label study, a higher incidence of borderline (less than 3 times the ULN), moderate (3 to 8 times the ULN), and marked (>8 times the ULN) elevations of ALT or AST was observed in patients receiving diclofenac when compared to other NSAIDs. Elevations in transaminases were seen more frequently in patients with osteoarthritis than in those with rheumatoid arthritis. Almost all meaningful elevations in transaminases were detected before patients became symptomatic.

Abnormal tests occurred during the first 2 months of therapy with oral diclofenac in 42 of the 51 patients in all trials who developed marked transaminase elevations. In postmarketing reports, cases of drug-induced hepatotoxicity have been reported in the first month, and in some cases, the first 2 months of NSAID therapy.

Postmarketing surveillance has reported cases of severe hepatic reactions, including liver necrosis, jaundice, fulminant hepatitis with and without jaundice, and liver failure. Some of these reported cases resulted in fatalities or liver transplantation.

In a European retrospective population-based, case-controlled study, 10 cases of oral diclofenac associated drug-induced liver injury with current use compared with non-use of diclofenac were associated with a statistically significant 4-fold adjusted odds ratio of liver injury. In this particular study, based on an overall number of 10 cases of liver injury associated with diclofenac, the adjusted odds ratio increased further with female gender, doses of 150 mg or more, and duration of use for more then 90 days.

Measure transaminases (ALT and AST) periodically in patients receiving long-term therapy with diclofenac, because severe hepatotoxicity may develop without a prodrome of distinguishing symptoms. The optimum times for making the first and subsequent transaminase measurements are not known. Based on clinical trial data and postmarketing experiences, monitor transaminases within 4 to 8 weeks after initiating treatment with diclofenac. However, severe hepatic reactions can occur at any time during treatment with diclofenac. If abnormal liver tests persist or worsen, if clinical signs and/or symptoms consistent with liver disease develop, or if systemic manifestations occur (e.g., eosinophilia, rash, abdominal pain, diarrhea, dark urine, etc.), discontinue PENNSAID immediately.

To minimize the possibility that hepatic injury will become severe between transaminase measurements, inform patients of the warning signs and symptoms of hepatotoxicity (e.g., nausea, fatigue, lethargy, diarrhea, pruritus, jaundice, right upper quadrant tenderness, and "flulike" symptoms), and the appropriate action to take if these signs and symptoms appear.

To minimize the potential risk for an adverse liver-related event in patients treated with PENNSAID, use the lowest effective dose for the shortest duration possible. Exercise caution when prescribing PENNSAID with concomitant drugs that are known to be potentially hepatotoxic (e.g., acetaminophen, certain antibiotics, antiepileptics). Caution patients to avoid taking unprescribed acetaminophen while using PENNSAID.

5.4 Hypertension

NSAIDs, including diclofenac, can lead to new onset or worsening of preexisting hypertension, either of which may contribute to the increased incidence of CV events. Use NSAIDs, including PENNSAID, with caution in patients with hypertension. Monitor blood pressure (BP) closely during the initiation of NSAID treatment and throughout the course of therapy.

Patients taking ACE-inhibitors, thiazides or loop diuretics may have impaired response to these therapies when taking NSAIDs.

5.5 Congestive Heart Failure and Edema

Fluid retention and edema have been observed in some patients treated with NSAIDs, including PENNSAID. Use PENNSAID with caution in patients with fluid retention or heart failure.

5.6 Renal Effects

Use caution when initiating treatment with PENNSAID in patients with considerable dehydration.

Long-term administration of NSAIDs has resulted in renal papillary necrosis and other renal injury. Renal toxicity has also been seen in patients in whom renal prostaglandins have a compensatory role in the maintenance of renal perfusion. In these patients, administration of an NSAID may cause a dose-dependent reduction in prostaglandin formation and, secondarily, in renal blood flow, which may precipitate overt renal decompensation. Patients at greatest risk of this reaction are those with impaired renal function, heart failure, liver dysfunction, those taking diuretics and ACE-inhibitors, and the elderly. Discontinuation of NSAID therapy is usually followed by recovery to the pretreatment state.

No information is available from controlled clinical studies regarding the use of PENNSAID in patients with advanced renal disease. Therefore, treatment with PENNSAID is not recommended in patients with advanced renal disease. If PENNSAID therapy is initiated, close monitoring of the patient's renal function is advisable.

5.7 Anaphylactoid Reactions

As with other NSAIDs, anaphylactoid reactions may occur in patients without prior exposure to PENNSAID. Do not prescribe PENNSAID to patients with the aspirin triad. This symptom complex typically occurs in asthmatic patients who experience rhinitis with or without nasal polyps, or who exhibit severe, potentially fatal bronchospasm after taking aspirin or other NSAIDs [see Contraindications (4) and Warnings and Precautions (5.10)]. Seek emergency help in cases where an anaphylactoid reaction occurs.

5.8 Skin Reactions

Do not apply PENNSAID to open skin wounds, infections, inflammations, or exfoliative dermatitis, as it may affect absorption and tolerability of the drug.

NSAIDs, including PENNSAID, can cause serious skin adverse events such as exfoliative dermatitis, Stevens-Johnson Syndrome (SJS), and toxic epidermal necrolysis (TEN), which can be fatal. These serious events may occur without warning. Inform patients about the signs and symptoms of serious skin manifestations, and discontinue use of the drug at the first appearance of skin rash or any other signs of hypersensitivity.

5.9 Pregnancy

PENNSAID should not be used by pregnant or nursing women or those intending to become pregnant.

5.10 Preexisting Asthma

Patients with asthma may have aspirin-sensitive asthma. The use of aspirin in patients with aspirin-sensitive asthma has been associated with severe bronchospasm, which can be fatal. Since cross-reactivity, including bronchospasm, between aspirin and other nonsteroidal anti-inflammatory drugs has been reported in such aspirin-sensitive patients, do not administer PENNSAID to patients with this form of aspirin sensitivity and use with caution in patients with preexisting asthma.

5.11 Sun Exposure

Instruct patients to avoid exposure to natural or artificial sunlight on treated knee(s) because studies in animals indicated topical diclofenac treatment resulted in an earlier onset of ultraviolet light-induced skin tumors. The potential effects of PENNSAID on skin response to ultraviolet damage in humans are not known.

5.12 Eye Exposure

Avoid contact of PENNSAID with eyes and mucosa. Advise patients that if eye contact occurs, immediately wash out the eye with water or saline and consult a physician if irritation persists for more than an hour.

5.13 Oral Nonsteroidal Anti-Inflammatory Drugs

Concomitant use of oral NSAIDs with PENNSAID resulted in a higher rate of rectal hemorrhage, more frequent abnormal creatinine, urea and hemoglobin. Therefore, do not use combination therapy with PENNSAID and an oral NSAID unless the benefit outweighs the risk and conduct periodic laboratory evaluations.

5.14 Corticosteroid Treatment

PENNSAID cannot be expected to substitute for corticosteroids or to treat corticosteroid insufficiency. Abrupt discontinuation of corticosteroids may lead to exacerbation of corticosteroid-response illness. For patients on prolonged corticosteroid therapy, taper slowly if a decision is made to discontinue corticosteroids.

5.15 Inflammation

The pharmacological activity of PENNSAID in reducing inflammation, and possibly fever, may diminish the utility of these diagnostic signs in detecting complications of presumed noninfectious, painful conditions.

5.16 Hematological Effects

The effects of PENNSAID on platelet function were studied in 10 healthy subjects administered 80 drops four times a day for 7 days. There was no significant change in platelet aggregation following one week of treatment [see Clinical Pharmacology (12.4)].

Anemia is sometimes seen in patients receiving NSAIDs. This may be due to fluid retention, occult or gross GI blood loss, or an incompletely described effect upon erythropoiesis. Check hemoglobin or hematocrit of patients on PENNSAID if they exhibit any signs or symptoms of anemia or blood loss.

NSAIDs inhibit platelet aggregation and have been shown to prolong bleeding time in some patients. Unlike aspirin, their effect on platelet function is quantitatively less, of shorter duration and reversible. Carefully monitor patients receiving PENNSAID who may be adversely affected by alterations in platelet function, such as those with coagulation disorders or patients receiving anticoagulants.

5.17 Monitoring

Because serious GI tract ulcerations and bleeding can occur without warning symptoms in patients taking NSAIDs, monitor patients for signs or symptoms of GI bleeding. Check CBC and a chemistry profile periodically in patients on long-term treatment with NSAIDs. Discontinue PENNSAID if abnormal liver tests or renal tests persist or worsen.

6. ADVERSE REACTIONS

6.1 Clinical Studies Experience

Because clinical trials are conducted under widely varying conditions, adverse reaction rates observed in the clinical trials of a drug cannot be directly compared to rates in the clinical trials of another drug and may not reflect the rates observed in practice.

The data described below reflect exposure to PENNSAID of 911 patients treated between 4 and 12 weeks (mean duration of 49 days) in seven Phase 3 controlled trials, as well as exposure of 793 patients treated in an open-label study, including 463 patients treated for at least 6 months, and 144 patients treated for at least 12 months. The population mean age was approximately 60 years, 89% of patients were Caucasians, 64% were females, and all patients had primary osteoarthritis. The most common adverse events with PENNSAID were application site skin reactions. These events were the most common reason for withdrawing from the studies.

Application site reactions:

In controlled trials, the most common treatment-related adverse events in patients receiving PENNSAID were application site skin reactions. Application site reactions were characterized by one or more of the following: dryness, erythema, induration, vesicles, paresthesia, pruritus, vasodilation, acne, and urticaria. The most frequent of these reactions were dry skin (32%), contact dermatitis characterized by skin erythema and induration (9%), contact dermatitis with vesicles (2%) and pruritus (4%). In one controlled trial, a higher rate of contact dermatitis with vesicles (4%) was observed after treatment of 152 subjects with the combination of PENNSAID and oral diclofenac. In the open label uncontrolled long-term safety study, contact dermatitis occurred in 13% and contact dermatitis with vesicles in 10% of patients, generally within the first 6 months of exposure, leading to a withdrawal rate for an application site event of 14%.

Adverse events common to the NSAID class:

In controlled trials, subjects treated with PENNSAID experienced some adverse events associated with the NSAID class more frequently than subjects using placebo (constipation, diarrhea, dyspepsia, nausea, flatulence, abdominal pain, edema; see Table 1). The combination of PENNSAID and oral diclofenac, compared to oral diclofenac alone, resulted in a higher rate of rectal hemorrhage (3% vs. less than 1%), and more frequent abnormal creatinine (12% vs. 7%), urea (20% vs. 12%), and hemoglobin (13% vs. 9%), but no difference in elevation of liver transaminases.

Table 1 lists all adverse reactions occurring in ≥1% of patients receiving PENNSAID, where the rate in the PENNSAID group exceeded placebo, from seven controlled studies conducted in patients with osteoarthritis. Since these trials were of different durations, these percentages do not capture cumulative rates of occurrence.

Table 1: Adverse Reactions occurring in ≥1% of patients treated with PENNSAID® in placebo and oral diclofenac-controlled trials.
Treatment Group: | PENNSAID® N=911 | Topical Placebo N=332
Adverse Reaction† | N (%) | N (%)
Dry Skin (Application Site) | 292 (32) | 17 (5)
Contact Dermatitis (Application Site) | 83 (9) | 6 (2)
Dyspepsia | 72 (8) | 13 (4)
Abdominal Pain | 54 (6) | 10 (3)
Flatulence | 35 (4) | 1 (<1)
Pruritus (Application Site) | 34 (4) | 7 (2)
Diarrhea | 33 (4) | 7 (2)
Nausea | 33 (4) | 3 (1)
Pharyngitis | 40 (4) | 13 (4)
Constipation | 29 (3) | 1 (<1)
Edema | 26 (3) | 0
Rash (Non-Application Site) | 25 (3) | 5 (2)
Infection | 25 (3) | 8 (2)
Ecchymosis | 19 (2) | 1 (<1)
Dry Skin (Non-Application Site) | 19 (2) | 1 (<1)
Contact Dermatitis, vesicles (Application Site) | 18 (2) | 0
Paresthesia (Non-Application Site) | 14 (2) | 3 (<1)
Accidental Injury | 22 (2) | 7 (2)
Pruritus (Non-Application Site) | 15 (2) | 2 (<1)
Sinusitis | 10 (1) | 2 (<1)
Halitosis | 11 (1) | 1 (<1)
Application Site Reaction (not otherwise specified) | 11 (1) | 3 (<1)
†Preferred Term according to COSTART

6.2 Postmarketing Experience

In non-US postmarketing surveillance, the following adverse reactions have been reported during post-approval use of PENNSAID. Because these reactions are reported voluntarily from a population of uncertain size, it is not always possible to reliably estimate their frequency or establish a causal relationship to drug exposure.
Body as a Whole: abdominal pain, accidental injury, allergic reaction, asthenia, back pain, body odor, chest pain, edema, face edema, halitosis, headache, lack of drug effect, neck rigidity, pain

Cardiovascular: palpitation, cardiovascular disorder

Digestive: diarrhea, dry mouth, dyspepsia, gastroenteritis, decreased appetite, mouth ulceration, nausea, rectal hemorrhage, ulcerative stomatitis

Metabolic and Nutritional: creatinine increased

Musculoskeletal: leg cramps, myalgia

Nervous: depression, dizziness, drowsiness, lethargy, paresthesia, paresthesia at application site

Respiratory: asthma, dyspnea, laryngismus, laryngitis, pharyngitis

Skin and Appendages: At the Application Site: contact dermatitis, contact dermatitis with vesicles, dry skin, pruritus, rash; Other Skin and Appendages Adverse Reactions: eczema, rash, pruritus, skin discoloration, urticaria

Special Senses: abnormal vision, blurred vision, cataract, ear pain, eye disorder, eye pain, taste perversion

7. DRUG INTERACTIONS

Drug interactions with the use of PENNSAID have not been studied. The following drug interactions [sections 7.1 to 7.7] are noted for oral diclofenac sodium.

7.1 Aspirin

When diclofenac is administered with aspirin, the binding of diclofenac to protein is reduced, although the clearance of free diclofenac is not altered. The clinical significance of this interaction is not known; however, as with other NSAIDs, concomitant administration of diclofenac and aspirin is not generally recommended because of the potential of increased adverse effects.

7.2 Anticoagulants

The effects of anticoagulants such as warfarin and NSAIDs on GI bleeding are synergistic, such that users of both drugs together have a risk of serious GI bleeding higher than users of either drug alone.

7.3 ACE-Inhibitors

NSAIDs may diminish the antihypertensive effect of angiotensin converting enzyme (ACE) inhibitors. Consider this interaction in patients taking NSAIDs concomitantly with ACE-inhibitors.

7.4 Diuretics

Clinical studies, as well as postmarketing observations, have shown that NSAIDs can reduce the natriuretic effect of furosemide and thiazides in some patients. The response has been attributed to inhibition of renal prostaglandin synthesis. During concomitant therapy with NSAIDs, observe the patient closely for signs of renal failure [see Warnings and Precautions (5.6)], as well as to assure diuretic efficacy.

7.5 Lithium

NSAIDs have produced an elevation of plasma lithium levels and a reduction in renal lithium clearance. The mean minimum lithium concentration increased 15% and the renal clearance was decreased by approximately 20%. These effects have been attributed to inhibition of renal prostaglandin synthesis by the NSAID. Thus, when NSAIDs, including diclofenac, and lithium are administered concurrently, observe patients carefully for signs of lithium toxicity.

7.6 Methotrexate

NSAIDs have been reported to competitively inhibit methotrexate accumulation in rabbit kidney slices. This may indicate that they could enhance the toxicity of methotrexate. Use caution when NSAIDs, including diclofenac, are administered concomitantly with methotrexate.

7.7 Cyclosporine

Diclofenac, like other NSAIDs, may affect renal prostaglandins and increase the toxicity of certain drugs. Therefore, concomitant therapy with diclofenac may increase cyclosporine’s nephrotoxicity. Use caution when diclofenac is administered concomitantly with cyclosporine.

7.8 Oral Nonsteroidal Anti-Inflammatory Drugs

Concomitant use of oral NSAIDs with PENNSAID has been evaluated in one Phase 3 controlled trial and in combination with oral diclofenac, compared to oral diclofenac alone, resulted in a higher rate of rectal hemorrhage (3% vs. less than 1%), and more frequent abnormal creatinine (12% vs. 7%), urea (20% vs. 12%) and hemoglobin (13% vs. 9%). Therefore, do not use combination therapy with PENNSAID and an oral NSAID unless the benefit outweighs the risk and conduct periodic laboratory evaluations.

7.9 Topical Treatments

Instruct patients that before applying sunscreen, insect repellant, lotion, moisturizer, cosmetics, or other topical medication to the same skin surface of the knee treated with PENNSAID, they must wait until the treated area is completely dry.

8. USE IN SPECIFIC POPULATIONS

8.1 Pregnancy

Pregnancy Category C prior to 30 weeks gestation; Category D starting 30 weeks gestation.
Teratogenic Effects:

There are no adequate and well-controlled studies of PENNSAID in pregnant women. PENNSAID should not be used by pregnant women as its safe use has not been adequately determined and starting at 30 weeks gestation, diclofenac and other NSAIDs should be avoided by pregnant women as premature closure of the ductus arteriosus in the fetus may occur. Developmental studies in animals demonstrated that diclofenac sodium administration did not produce teratogenicity despite the induction of maternal toxicity and fetal toxicity in mice at doses up to 20 mg/kg/day (0.6-fold the maximum recommended human dose [MRHD] of 154 mg/day based on body surface area comparison), and in rats and rabbits at doses up to 10 mg/kg/day (approximately 0.6-fold and 1.3-fold the MRHD, respectively). Published reproductive and developmental studies of dimethyl sulfoxide (DMSO, the solvent used in PENNSAID) are equivocal as to potential teratogenicity.

Nonteratogenic Effects:

In rats, maternally toxic doses of diclofenac were associated with dystocia, prolonged gestation, reduced fetal weights and growth, and reduced fetal survival.

8.2 Labor and Delivery

The effects of PENNSAID on labor and delivery in pregnant women are unknown. In rat studies maternal exposure to diclofenac, as with other NSAID drugs, known to inhibit prostaglandin synthesis, increased the incidence of dystocia, delayed parturition, and decreased offspring survival.

8.3 Nursing Mothers

It is not known whether this drug is excreted in human milk; however, there is a case report in the literature indicating that diclofenac can be detected at low levels in breast milk. Because many drugs are excreted in human milk and because of the potential for serious adverse reactions in nursing infants from PENNSAID, a decision should be made whether to discontinue nursing or to discontinue the drug, taking into account the importance of the drug to the mother.

8.4 Pediatric Use

Safety and effectiveness in pediatric patients have not been established.

8.5 Geriatric Use

Of the 911 patients treated with PENNSAID in seven controlled, Phase 3 clinical trials, 444 subjects were 65 years of age and over. There was no age-related difference in the incidence of adverse events. Of the 793 patients treated with PENNSAID in one open-labeled safety trial, 334 subjects were 65 years of age and over including 107 subjects 75 and over. There was no difference in the incidence of adverse events with long-term exposure to PENNSAID for this elderly population. As with any NSAID, use caution in treating the elderly (65 years and older) and it may be useful to monitor renal function since they are more likely to have decreased baseline renal function.

10. OVERDOSAGE

There have been no known experiences of overdose with PENNSAID.

Symptoms following acute NSAID overdose are usually limited to lethargy, drowsiness, nausea, vomiting, and epigastric pain, which are generally reversible with supportive care. Gastrointestinal bleeding can occur. Hypertension, acute renal failure, respiratory depression and coma may occur, but are rare. Anaphylactoid reactions have been reported with therapeutic ingestion of NSAIDs, and may occur following an overdose.

Manage patients using symptomatic and supportive care following an NSAID overdose. There are no specific antidotes. Emesis is not recommended due to a possibility of aspiration and subsequent respiratory irritation by DMSO contained in PENNSAID. Activated charcoal (60 to 100 g in adults, 1 to 2 g/kg in children) and/or osmotic cathartic may be indicated in patients seen within 4 hours of ingestion with symptoms or following a large overdose (5 to 10 times the usual dose). Forced diuresis, alkalinization of urine, hemodialysis, or hemoperfusion may not be useful due to high protein binding.

For additional information about overdose treatment, call a poison control center (1-800-222-1222).

11. DESCRIPTION

PENNSAID is a clear, colorless to faintly pink-orange solution for topical application.

PENNSAID contains 1.5% w/w diclofenac sodium, a benzeneacetic acid derivative that is a nonsteroidal anti-inflammatory drug (NSAID), designated chemically as 2-[(2,6-dichlorophenyl)amino]-benzeneacetic acid, monosodium salt. The molecular weight is 318.14. Its molecular formula is C14H10Cl2NNaO2 and it has the following structural formula:

Each 1 mL of solution contains 16.05 mg of diclofenac sodium. In addition, PENNSAID contains the following inactive ingredients: dimethyl sulfoxide USP (DMSO, 45.5% w/w), propylene glycol, alcohol, glycerin and purified water.

12. CLINICAL PHARMACOLOGY

12.1 Mechanism of Action

The mechanism of action of diclofenac is similar to that of other nonsteroidal anti-inflammatory drugs. Diclofenac inhibits the enzyme, cyclooxygenase (COX), an early component of the arachidonic acid cascade, resulting in the reduced formation of prostaglandins, thromboxanes and prostacylin. It is not completely understood how reduced synthesis of these compounds results in therapeutic efficacy.

12.2 Pharmacodynamics

Diclofenac, the active component of PENNSAID has anti-inflammatory, anti-nociception, and antipyretic effects.

12.3 Pharmacokinetics

After topical administration to healthy human volunteers of single and multiple maximum doses of PENNSAID, 40 drops (approximately 1.2 mL) to each knee (80 drops total dose), the following diclofenac pharmacokinetic parameters were obtained: (see Table 2).

Table 2: Single-Dose (80 drops) and Multiple Dose (80 drops four times daily for 7 days) PENNSAID Pharmacokinetic Parameters
Pharmacokinetic Parameters | Diclofenac sodium
Pharmacokinetic Parameters | Normal Adults [N=18] (Age: 18-55 years) | Normal Adults [N=19] (Age: 18-55 years)
Pharmacokinetic Parameters | Single Dose | Multiple Dose Four times daily for 7 days
AUC0-t | 177.5 ± 72.6 ng.h/mL | 695.4 ± 348.9 ng.h/mL
AUC0-inf | 196.3 ± 68.5 ng.h/mL | 745.2 ± 374.7 ng.h/mL
Plasma Cmax | 8.1 ± 5.9 ng/mL | 19.4 ± 9.3 ng/mL
Plasma Tmax (h) | 11.0 ± 6.4 | 4.0 ± 6.5
Plasma t1/2 (h) | 36.7 ± 20.8 | 79.0 ± 38.1
Kel (h^-1) | 0.024 ± 0.010 | 0.011 ± 0.004
CL/F (L/h) | 244.7 ± 84.7^1 | --
^1Apparent total body clearance

Absorption
Diclofenac systemic exposure from PENNSAID application (4 times daily for 1 week) was approximately 1/3 of the diclofenac systemic exposure from the Solaraze (diclofenac topical gel) application (twice daily for 4 weeks).
Distribution
Diclofenac is more than 99% bound to human serum proteins, primarily to albumin.
Diclofenac diffuses into and out of the synovial fluid. Diffusion into the joint occurs when plasma levels are higher than those in the synovial fluid, after which the process reverses and synovial fluid levels are higher than plasma levels. It is not known whether diffusion into the joint plays a role in the effectiveness of diclofenac.
Metabolism
Five diclofenac metabolites have been identified in human plasma and urine. The metabolites include 4'-hydroxy-, 5-hydroxy-, 3'-hydroxy-, 4',5-dihydroxy- and 3'-hydroxy-4'-methoxy diclofenac. The major diclofenac metabolite, 4'-hydroxy-diclofenac, has very weak pharmacologic activity. The formation of 4'-hydroxy diclofenac is primarily mediated by CPY2C9. Both diclofenac and its oxidative metabolites undergo glucuronidation or sulfation followed by biliary excretion. Acylglucuronidation mediated by UGT2B7 and oxidation mediated by CPY2C8 may also play a role in diclofenac metabolism. CYP3A4 is responsible for the formation of minor metabolites, 5-hydroxy and 3'-hydroxy-diclofenac.
Excretion
Diclofenac is eliminated through metabolism and subsequent urinary and biliary excretion of the glucuronide and the sulfate conjugates of the metabolites.
Little or no free unchanged diclofenac is excreted in the urine.
Special Populations
Pediatric: The pharmacokinetics of PENNSAID has not been investigated in pediatric patients.
Race: Pharmacokinetic differences due to race have not been studied.

12.4 Platelets

The effect of PENNSAID on platelet function was evaluated in 10 healthy human volunteers as a sub-study of a multiple-dose pharmacokinetic study [see Pharmacokinetics (12.3)]. Average (range) platelet aggregation time following stimulation with adenosine diphosphate, collagen, epinephrine and arachidonic acid was 101.3% (73.3 to 128.1), 99.8% (69.6 to 112.9), 109.9% (66.2 to 178.1) and 99.0% (15.5 to 126.6) of baseline value, respectively. These results indicate that there was no effect on platelet aggregation after application of the maximum clinical dose for 7 days [see Pharmacokinetics (12.3)].

13. NONCLINICAL TOXICOLOGY

13.1 Carcinogenesis, Mutagenesis, Impairment of Fertility

Carcinogenicity studies in mice and rats administered diclofenac sodium as a dietary constituent for 2 years resulted in no significant increases in tumor incidence at doses up to 2 mg/kg/day corresponding to approximately 0.35- and 0.7-fold (mouse and rat, respectively) of the maximum recommended human topical dose (MRHD) of PENNSAID (based on apparent bioavailability and body surface area comparison).

In a dermal carcinogenicity study conducted in albino mice, daily topical applications of diclofenac sodium for two years at concentrations up to 0.035% diclofenac sodium (a 43-fold lower diclofenac sodium concentration than present in PENNSAID) did not increase neoplasm incidence.

In a photococarcinogenicity study conducted in hairless mice, topical application of diclofenac sodium at doses up to 0.035% diclofenac sodium (a 43-fold lower diclofenac sodium concentration than present in PENNSAID) resulted in an earlier median time of onset of tumors.

Mutagenesis: Diclofenac was not mutagenic or clastogenic in a battery of genotoxicity tests that included the bacterial reverse mutation assay, in vitro mouse lymphoma point mutation assay, chromosomal aberration studies in Chinese hamster ovarian cells in vitro, and in vivo rat chromosomal aberration assay of bone marrow cells.

Impairment of Fertility: Fertility studies have not been conducted with PENNSAID. Diclofenac sodium administered to male and female rats at doses up to 4 mg/kg/day (1.4-fold of the MRHD of PENNSAID based on apparent bioavailability and body surface area comparison) did not affect fertility. Studies have not been conducted to determine the safety of DMSO on fertility.

13.2 Animal Toxicology and/or Pharmacology

Ocular Effects

No adverse effects were observed using indirect ophthalmoscopy after multiple-daily dermal application to rats for 26 weeks and minipigs for 52 weeks of DMSO at twice the concentration found in PENNSAID. Published studies of dermal or oral administration of DMSO to rabbits, dogs and pigs described refractive changes of lens curvature and cortical fibers indicative of myopic changes and/or incidences of lens opacity or discoloration when evaluated using slit-lamp biomicroscopy examination, although no ocular abnormalities were observed in rhesus monkeys during daily oral or dermal treatment with DMSO for 9 to 18 months.

14. CLINICAL STUDIES

14.1 Pivotal Studies in Osteoarthritis of the Knee

The use of PENNSAID for the treatment of the signs and symptoms of osteoarthritis of the knee was evaluated in two double-blind controlled trials conducted in the US and Canada, involving patients treated with PENNSAID at a dose of 40 drops four times a day for 12 weeks. PENNSAID was compared to topical placebo (2.3% DMSO with other excipients) and/or topical vehicle solution (45.5% w/w DMSO with other excipients), applied directly to the study knee. In both trials, PENNSAID treatment resulted in statistically significant clinical improvement compared to placebo and/or vehicle, in all three primary efficacy variables―pain, physical function (Western Ontario and McMaster Universities LK3.1 OA Index (WOMAC) pain and physical function dimensions) and Patient Overall Health Assessment (POHA)/Patient Global Assessment (PGA). Numerical results are summarized in Tables 3 and 4.

Table 3: Change in treatment outcomes after 12 weeks of treatment in one study of efficacy of PENNSAID®
Efficacy Variable | Study I Mean baseline score and mean change in efficacy variables after 12 weeks of treatment
Efficacy Variable | Mean Baseline score | PENNSAID® N=154 | Topical placebo^1 N=155 | Topical vehicle^2 N=161
WOMAC pain score (Likert 3.1, 0–20) | 13 | -6.0 | -4.7 | -4.7
WOMAC physical function (Likert 3.1, 0–68) | 42 | -15.7 | -12.3 | -12.1
POHA (0–4) | 2.3 | -1.0 | -0.4 | -0.6
^1placebo formulation included 2.3% DMSO
^2vehicle formulation included 45.5% DMSO

Table 4: Change in treatment outcomes after 12 weeks of treatment in one study of efficacy of PENNSAID
Efficacy Variable | Study II Mean baseline score and mean change in efficacy variables after 12 weeks of treatment
Efficacy Variable | Mean Baseline score | PENNSAID N=164 | Topical vehicle^1 N=162
WOMAC pain score (Likert 3.1, 0–20) | 13 | -5.9 | -4.4
WOMAC physical function (Likert 3.1, 0–68) | 42 | -15.3 | -10.3
PGA (0–4) | 3.1 | -1.3 | -1.0
^1vehicle formulation included 45.5% DMSO

16. HOW SUPPLIED/STORAGE AND HANDLING

PENNSAID is supplied as a clear, colorless to faintly pink-orange solution containing 16.05 mg of diclofenac sodium per mL of solution, in a white high density polyethylene bottle with a white low-density dropper cap.

NDC Number & Size

15 mL bottle (physician sample) | NDC # 23635-310-11
150 mL bottle | NDC # 23635-310-15

Storage
Store at 25°C (77°F); excursions permitted to 15° to 30°C (59° to 86°F) [See USP Controlled Room Temperature].

17. PATIENT COUNSELING INFORMATION

See FDA-Approved Medication Guide (17.10) for specific patient instructions.

17.1 Patient/Caregiver Instructions

Inform patients of the following information before initiating therapy with an NSAID and periodically during the course of ongoing therapy. Encourage patients to read the NSAID Medication Guide that accompanies each prescription dispensed prior to using PENNSAID [see Medication Guide (17.10) and Patient Instructions for Use (17.11)].

17.2 Cardiovascular Effects

PENNSAID, like other NSAIDs, may cause serious CV side effects, such as MI or stroke, which may result in hospitalization and even death. Although serious CV events can occur without warning symptoms, instruct patients to be alert for the signs and symptoms of chest pain, shortness of breath, weakness, slurring of speech, and to ask for medical advice when observing any indicative sign or symptoms. Inform patients of the importance of this follow-up [see Warnings and Precautions (5.1)].

17.3 Gastrointestinal Effects

PENNSAID, like other NSAIDs, may cause GI discomfort and, rarely, serious GI side effects, such as ulcers and bleeding, which may result in hospitalization and even death. Although serious GI tract ulcerations and bleeding can occur without warning symptoms, inform patients to be alert for the signs and symptoms of ulceration and bleeding, and to ask for medical advice when observing any indicative sign or symptoms including epigastric pain, dyspepsia, melena, and hematemesis. Instruct patients of the importance of this follow-up [see Warnings and Precautions (5.2)].

17.4 Hepatotoxicity

Inform patients of the warning signs and symptoms of hepatotoxicity (e.g., nausea, fatigue, lethargy, pruritus, jaundice, right upper quadrant tenderness, and “flu-like” symptoms). If these occur, instruct patients to stop therapy with PENNSAID and seek immediate medical therapy [see Warnings and Precautions (5.3)].

17.5 Adverse Skin Reactions

PENNSAID, like other NSAIDs, can cause serious systemic skin side effects such as exfoliative dermatitis, SJS, and TEN, which may result in hospitalizations and even death. Although serious systemic skin reactions may occur without warning, instruct patients to be alert for the signs and symptoms of skin rash and blisters, fever, or other signs of hypersensitivity such as itching, and to ask for medical advice when observing any indicative signs or symptoms [see Warnings and Precautions (5.8)].

Advise patients to stop PENNSAID immediately if they develop any type of generalized rash and contact their physicians as soon as possible.

PENNSAID can cause a localized skin reaction at the application site. Advise patients to contact their physicians as soon as possible if they develop any type of localized application site rash.

Instruct patients not to apply PENNSAID to open skin wounds, infections, inflammations, or exfoliative dermatitis, as it may affect absorption and reduce tolerability of the drug.

Instruct patients to wait until the area treated with PENNSAID is completely dry before applying sunscreen, insect repellant, lotion, moisturizer, cosmetics, or other topical medication.

Instruct patients to minimize or avoid exposure of treated knee(s) to natural or artificial sunlight.

17.6 Weight Gain and Edema

Instruct patients to promptly report to their physician signs or symptoms of unexplained weight gain or edema following treatment with PENNSAID [see Warnings and Precautions (5.5)].

17.7 Anaphylactoid Reactions

Inform patients of the signs of an anaphylactoid reaction (e.g., difficulty breathing, swelling of the face or throat). If these occur, instruct patients to seek immediate emergency help [see Warnings and Precautions (5.7)].

17.8 Effects During Pregnancy

Instruct patients who are pregnant or intending to become pregnant not to use PENNSAID [see Use in Specific Populations (8.1) and Impairment of Fertility (13.1)].

17.9 Eye Exposure

Instruct patients to avoid contact of PENNSAID with the eyes and mucosa. Advise patients that if eye contact occurs, immediately wash out the eye with water or saline and consult a physician if irritation persists for more than an hour.

17.10 Medication Guide

Medication Guide For Non-Steroidal Anti-Inflammatory Drugs (NSAIDs)

(See the end of this Medication Guide for a list of prescription NSAID medicines.)

What is the most important information I should know about medicines called Non-Steroidal Anti-Inflammatory Drugs (NSAIDs)?

NSAID medicines may increase the chance of a heart attack or stroke that can lead to death.
This chance increases:

- with longer use of NSAID medicines
- in people who have heart disease

NSAID medicines should never be used right before or after a heart surgery called a “coronary artery bypass graft (CABG).”

NSAID medicines can cause ulcers and bleeding in the stomach and intestines at any time during treatment. Ulcers and bleeding:

- can happen without warning symptoms
- may cause death

The chance of a person getting an ulcer or bleeding increases with:

- taking medicines called “corticosteroids” and “anticoagulants”
- longer use
- smoking
- drinking alcohol
- older age
- having poor health

NSAID medicines should only be used:

- exactly as prescribed
- at the lowest dose possible for your treatment
- for the shortest time needed

What are Non-Steroidal Anti-Inflammatory Drugs (NSAIDs)?

NSAID medicines are used to treat pain and redness, swelling, and heat (inflammation) from medical conditions such as:

- different types of arthritis
- menstrual cramps and other types of short-term pain

Who should not take a Non-Steroidal Anti-Inflammatory Drug (NSAID)?

Do not take an NSAID medicine:

- if you had an asthma attack, hives, or other allergic reaction with aspirin or any other NSAID medicine
- for pain right before or after heart bypass surgery

Tell your healthcare provider:

- about all of your medical conditions.
- about all of the medicines you take. NSAIDs and some other medicines can interact with each other and cause serious side effects. Keep a list of your medicines to show to your healthcare provider and pharmacist.
- if you are pregnant. NSAID medicines should not be used by pregnant women late in their pregnancy.
- if you are breastfeeding. Talk to your doctor.

What are the possible side effects of Non-Steroidal Anti-Inflammatory Drugs (NSAIDs)?

Serious side effects include:

- heart attack
- stroke
- high blood pressure
- heart failure from body swelling (fluid retention)
- kidney problems including kidney failure
- bleeding and ulcers in the stomach and intestine
- low red blood cells (anemia)
- life-threatening skin reactions
- life-threatening allergic reactions
- liver problems including liver failure
- asthma attacks in people who have asthma

Other side effects include:

- stomach pain
- constipation
- diarrhea
- gas
- heartburn
- nausea
- vomiting
- dizziness

Get emergency help right away if you have any of the following symptoms:

- shortness of breath or trouble breathing
- chest pain
- slurred speech
- weakness in one part or side of your body
- swelling of the face or throat

Stop your NSAID medicine and call your healthcare provider right away if you have any of the following symptoms:

- nausea
- more tired or weaker than usual
- itching
- your skin or eyes look yellow
- stomach pain
- flu-like symptoms
- vomit blood
- there is blood in your bowel movement or it is black and sticky like tar
- unusual weight gain
- skin rash or blisters with fever
- swelling of the arms and legs, hands and feet

These are not all the side effects with NSAID medicines. Talk to your healthcare provider or pharmacist for more information about NSAID medicines.

Call your doctor for medical advice about side effects. You may report side effects to FDA at 1-800-FDA-1088.

Other information about Non-Steroidal Anti-Inflammatory Drugs (NSAIDs):

- Aspirin is an NSAID medicine but it does not increase the chance of a heart attack. Aspirin can cause bleeding in the brain, stomach, and intestines. Aspirin can also cause ulcers in the stomach and intestines.
- Some of these NSAID medicines are sold in lower doses without a prescription (over-the-counter). Talk to your healthcare provider before using over-the-counter NSAIDs for more than 10 days.

NSAID medicines that need a prescription

Generic Name | Tradename
Celecoxib | Celebrex®
Diclofenac | Flector, Cataflam®, Voltaren®, Arthrotec™ (combined with misoprostol), PENNSAID®
Diflunisal | Dolobid®
Etodolac | Lodine®, Lodine®XL
Fenoprofen | Nalfon®, Nalfon®200
Flurbirofen | Ansaid®
Ibuprofen | Motrin®, Tab- Profen®, Vicoprofen®* (combined with hydrocodone), Combunox™ (combined with oxycodone)
Indomethacin | Indocin®, Indocin®SR, Indo-Lemmon™, Indomethagan™
Ketoprofen | Oruvail®
Ketorolac | Toradol®
Mefenamic Acid | Ponstel®
Meloxicam | Mobic®
Nabumetone | Relafen®
Naproxen | Naprosyn®, Anaprox®, Anaprox®DS, EC-Naproxyn®, Naprelan®, Naprapac® (copackaged with lansoprazole)
Oxaprozin | Daypro®
Piroxicam | Feldene®
Sulindac | Clinoril®
Tolmetin | Tolectin®, Tolectin DS®, Tolectin®600
*Vicoprofen contains the same dose of ibuprofen as over-the-counter (OTC) NSAID, and is usually used for less than 10 days to treat pain. The OTC NSAID label warns that long term continuous use may increase the risk of heart attack or stroke.

This Medication Guide has been approved by the U.S. Food and Drug Administration.

17.11 Patient Instructions for Use

Patient Instructions for Use
PENNSAID [pen/sed]
(diclofenac sodium topical solution)

Your doctor has prescribed PENNSAID® to treat your pain from osteoarthritis in your knee(s) and help you manage your daily activities better.

Before you use PENNSAID®:

- Apply PENNSAID® exactly as your doctor tells you. Do not apply PENNSAID® anywhere on your body other than where your doctor tells you.
- Apply PENNSAID® on clean, dry skin that does not have any cuts, infections or rashes.
- Use PENNSAID® 4 times each day on your knee(s).
- Do not get PENNSAID® in your eyes, nose or mouth. Only use PENNSAID® on your skin (topical use). If you get PENNSAID® in your eyes, rinse your eyes right away with water or saline. Call your doctor if your eyes are irritated for more than one hour.

Steps for using PENNSAID®:

Step 1. Wash your hands with soap and water before and after applying PENNSAID®.
Step 2. Your total dose for each knee is 40 drops of PENNSAID®. You will use 10 drops at a time. Put 10 drops of PENNSAID® either on your hand or directly on your knee.
Figure 1. Dispense 10 drops of PENNSAID® at a time

Step 3. Spread PENNSAID® evenly on the front, back and sides of your knee. Repeat this step 4 times so that your knee is completely covered with a total of 40 drops of PENNSAID®.
Figure 2. Spread PENNSAID® evenly on the front, and sides of your knee
Figure 3. Spread PENNSAID® evenly on the back of your knee

Step 4. Repeat steps 2 and 3 for the other knee if needed.

After you use PENNSAID®:
Do not

- cover your knee with clothing until your knee is completely dry
- put sunscreen, insect repellant, lotion, moisturizer, cosmetics, or other topical medicines on your knee until it is completely dry
- take a shower or a bath for at least 30 minutes after you put PENNSAID® on your knee(s)
- use heating pads or apply bandages to the skin where you have applied PENNSAID®
- expose your skin to sunlight or artificial light (tanning booths) where you have put PENNSAID®

How should I store PENNSAID®?

- Store PENNSAID® between 59°F to 86°F (15°C to 30°C).

Keep PENNSAID® and all medicines out of the reach of children.

COVIDIEN, COVIDIEN with logo and Covidien logo are U.S. and/or internationally registered trademarks of Covidien AG. PENNSAID is a trademark of Nuvo Research Inc. Other brands are trademarks of their respective owners.

Distributed by:
Mallinckrodt Brand Pharmaceuticals, Inc.
Hazelwood, MO 63042 USA

Manufactured by:
Nuvo Manufacturing
Varennes, Quebec, J3X 1P7 Canada
Issued 01/2010
E0073-01
Mallinckrodt
COVIDIEN™

PACKAGE LABEL

PENNSAID LABEL IMAGE